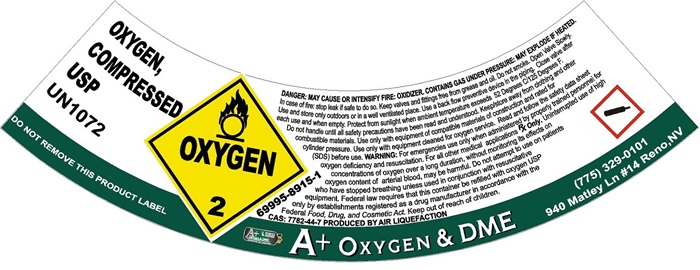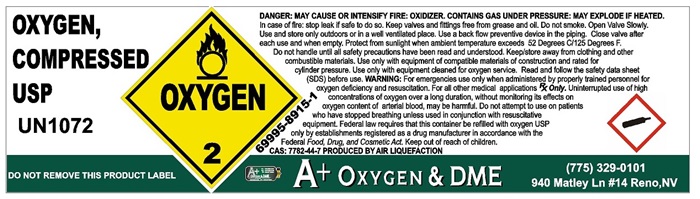 DRUG LABEL: Oxygen Compressed
NDC: 69995-8915 | Form: GAS
Manufacturer: A + OXYGEN & D.M.E.
Category: prescription | Type: HUMAN PRESCRIPTION DRUG LABEL
Date: 20241002

ACTIVE INGREDIENTS: OXYGEN 992 mL/100 mL

Oxygen

Oxygen

OXYGEN, COMPRESSED USP UN1072

DO NOT REMOVE THIS PRODUCT LABEL

OXYGEN 2

69995-8915-1

DANGE: MAY CAUSE OR INTENSIFY FIRE: OXIDIZER, CONTAINS GAS UNDER PRESSURE: MAY EXPLODE IF HEATED. In case of fire: stop leak if safe to do so. Keep valves and fittings free from grease and oil. Do not smoke. Open valve slowly. Use and store only outdoors or in a well-ventilated place. Use a back-flow preventive device in the piping. Close valve after each use and when empty. Protect from sunlight when ambient temperature exceeds 52 Degrees C/125 Degrees F. Do not handle until all safety precautions have been read and understood. Keep/store away from clothing and other combustible materials. Use only with equipment of compatible materials of construction and rated for cylinder pressure. Use only with equipment cleaned for oxygen service. Read and follow the safety data sheet (SDS) before use. WARNING: For emergencies use only when administered by properly trained personnel for oxygen deficiency and resuscitation. For all other medical applications Rx Only. Uninterrupted use of high concentrations of oxygen over a long duration, without monitoring its effects on oxygen content of arterial blood, may be harmful. Do not attempt to use on patients who have stopped breathing unless used in conjunction with resuscitative equipment. Federal law requires that this container be refilled with oxygen USP only by establishments registered as a drug manufacturer in accordance with the Federal Food, Drug and Cosmetic Act. Keep out of reach of children. CAS 7782-44-7 PRODUCED BY AIR LIQUEFACTION

A+ OXYGEN & DME

(775)329-0101

940 Matley Ln #14 Reno, NV